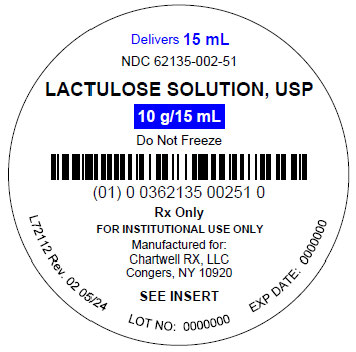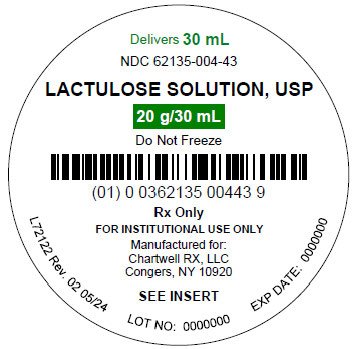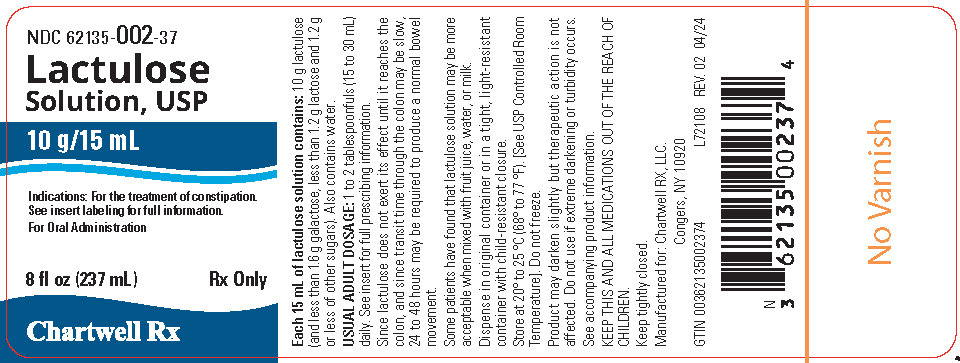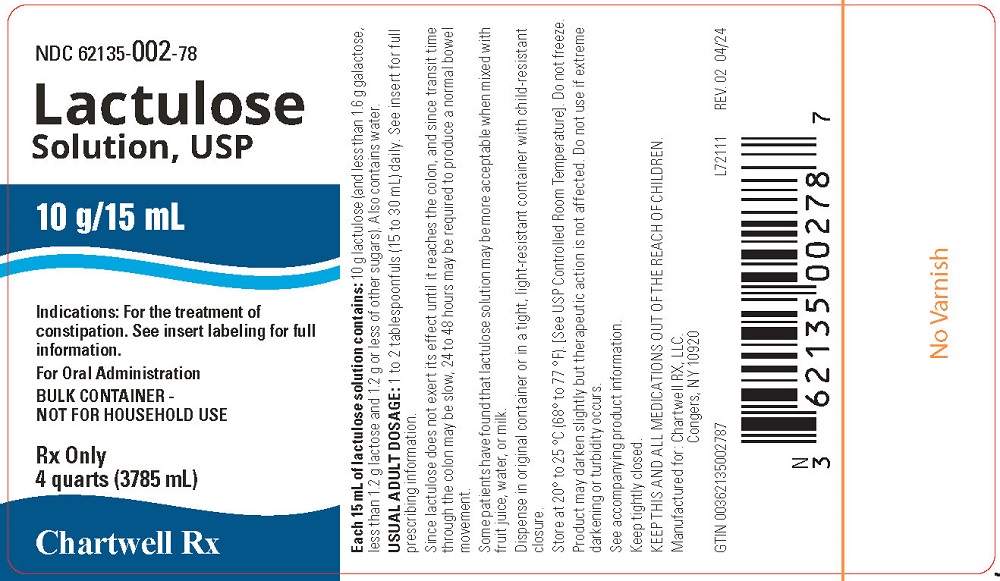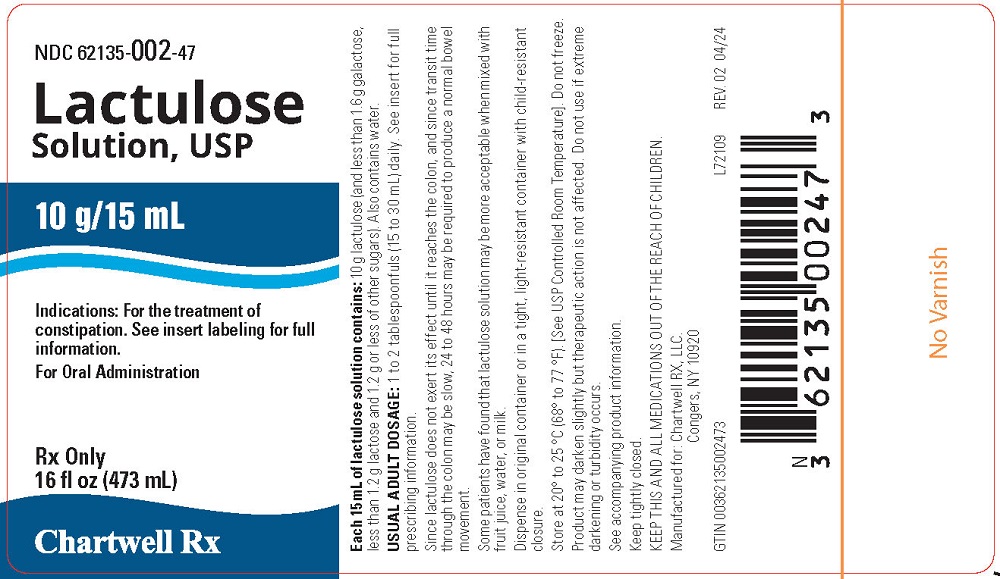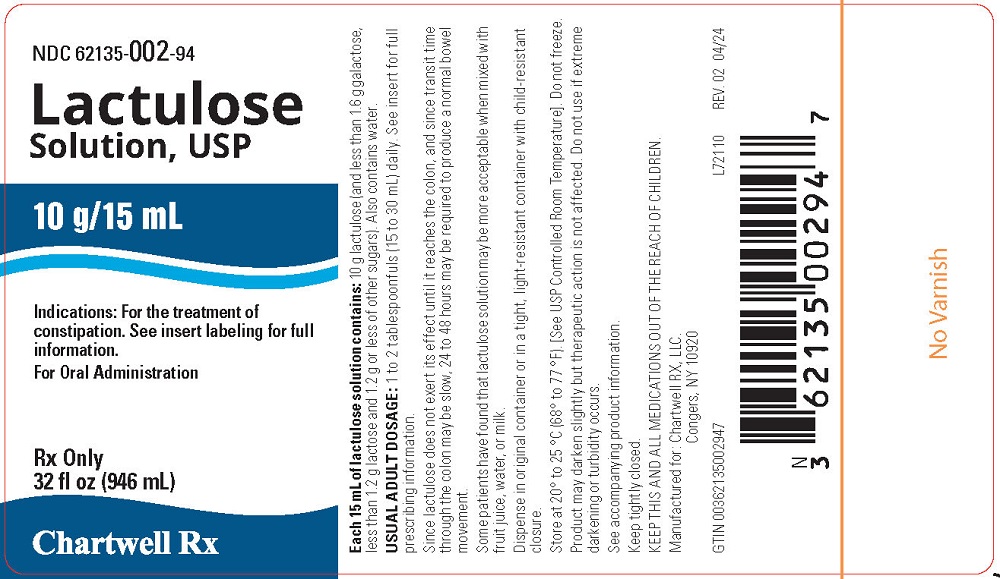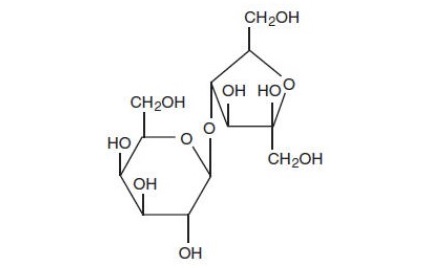 DRUG LABEL: Lactulose
NDC: 62135-002 | Form: SOLUTION
Manufacturer: Chartwell RX, LLC
Category: prescription | Type: HUMAN PRESCRIPTION DRUG LABEL
Date: 20260128

ACTIVE INGREDIENTS: LACTULOSE 10 g/15 mL

Lactulose Solution, USP
For Oral Administration
Rx ONLY

DESCRIPTION

Lactulose is a synthetic disaccharide in solution form for oral administration. Each 15 mL of Lactulose Solution, USP contains: 10 g lactulose (and less than 1.6 g galactose, less than 1.2 g lactose, and 1.2 g or less of other sugars). Also contains water. The pH range is 2.5 to 6.5.

Lactulose is a colonic acidifier which promotes laxation.

The chemical name for lactulose is 4-O-β-D-galactopyranosyl-D-fructofuranose. The molecular formula is C12H22O11. It has the following structural formula:

The molecular weight is 342.30. It is freely soluble in water.

CLINICAL PHARMACOLOGY

Lactulose is poorly absorbed from the gastrointestinal tract and no enzyme capable of hydrolysis of this disaccharide is present in human gastrointestinal tissue. As a result, oral doses of lactulose reach the colon virtually unchanged. In the colon, lactulose is broken down primarily to lactic acid, and also to small amounts of formic and acetic acids, by the action of colonic bacteria, which results in an increase in osmotic pressure and slight acidification of the colonic contents. This in turn causes an increase in stool water content and softens the stool.

Since lactulose does not exert its effect until it reaches the colon, and since transit time through the colon may be slow, 24 to 48 hours may be required to produce the desired bowel movement.

Lactulose given orally to man and experimental animals resulted in only small amounts reaching the blood. Urinary excretion has been determined to be 3% or less and is essentially complete within 24 hours.

INDICATION AND USAGE

For the treatment of constipation. In patients with a history of chronic constipation, lactulose solution therapy increases the number of bowel movements per day and the number of days on which bowel movements occur.

CONTRAINDICTIONS

Since lactulose solution contains galactose (less than 1.6 g/15 mL), it is contraindicated in patients who require a low galactose diet.

WARNINGS

A theoretical hazard may exist for patients being treated with lactulose solution who may be required to undergo electrocautery procedures during proctoscopy or colonoscopy. Accumulation of H2gas in significant concentration in the presence of an electrical spark may result in an explosive reaction. Although this complication has not been reported with lactulose, patients on lactulose therapy undergoing such procedures should have a thorough bowel cleansing with a non-fermentable solution. Insufflation of CO2as an additional safeguard may be pursued but is considered to be a redundant measure.

PRECAUTIONS

General

Since lactulose solution contains galactose (less than 1.6 g/15 mL) and lactose (less than 1.2 g/15 mL) it should be used with caution in diabetics.

Information for Patients

In the event that an unusual diarrheal condition occurs, contact your physician.

Laboratory Tests

Elderly, debilitated patients who receive lactulose for more than six months should have serum electrolytes (potassium, chloride, carbon dioxide) measured periodically.

Drug Interactions

Results of preliminary studies in humans and rats suggest that non-absorbable antacids given concurrently with lactulose may inhibit the desired lactulose-induced drop in colonic pH. Therefore, a possible lack of desired effect of treatment should be taken into consideration before such drugs are given concomitantly with lactulose solution.

Carcinogenesis, Mutagenesis, Impairment of Fertility

There are no known human data on long-term potential for carcinogenicity, mutagenicity, or impairment of fertility.

There are no known animal data on long-term potential for mutagenicity.

Administration of lactulose solution in the diet of mice for 18 months in concentrations of 3 and 10 percent (v/w) did not produce any evidence of carcinogenicity.

In studies of mice, rats, and rabbits, doses of lactulose solution up to 6 or 12 mL/kg/day produced no deleterious effects in breeding, conception, or parturition.

Pregnancy

Teratogenic Effects

Reproduction studies have been performed in mice, rats, and rabbits at doses up to 3 or 6 times the usual human oral dose and have revealed no evidence of impaired fertility or harm to the fetus due to lactulose. There are, however, no adequate and well-controlled studies in pregnant women. Because animal reproduction studies are not always predictive of human response, this drug should be used during pregnancy only if clearly needed.

Nursing Mothers

It is not known whether this drug is excreted in human milk. Because many drugs are excreted in human milk, caution should be exercised when lactulose solution is administered to a nursing woman.

Pediatric Use

Safety and effectiveness in pediatric patients have not been established.

ADVERSE REACTIONS

Precise frequency data are not available.

Initial dosing may produce flatulence and intestinal cramps, which are usually transient. Excessive dosage can lead to diarrhea with potential complications such as loss of fluids, hypokalemia, and hypernatremia.

Nausea and vomiting have been reported.

To report SUSPECTED ADVERSE REACTIONS, contact Chartwell RX, LLC. at 1-845-232-1683 or FDA at 1-800-FDA-1088 or www.fda.gov/medwatch.

OVERDOSAGE

Signs and Symptoms: There have been no reports of accidental overdosage. In the event of overdosage, it is expected that diarrhea and abdominal cramps would be the major symptoms. Medication should be terminated.

Oral LD50: The acute oral LD50of the drug is 48.8 mL/kg in mice and greater than 30 mL/kg in rats.

Dialysis: Dialysis data are not available for lactulose. Its molecular similarity to sucrose, however, would suggest that it should be dialyzable.

DOSAGE AND ADMINISTRATION

The usual dose is 1 to 2 tablespoonfuls (15 to 30 mL, containing 10 g to 20 g of lactulose) daily. The dose may be increased to 60 mL daily if necessary. Twenty-four to 48 hours may be required to produce a normal bowel movement.

Note: Some patients have found that lactulose solution may be more acceptable when mixed with fruit juice, water or milk.

HOW SUPPLIED

Lactulose Solution, USP is a colorless to amber syrupy liquid. It is available in

8 fl oz (237 mL) bottle (NDC 62135-002-37)

16 fl oz (473 mL) bottle (NDC 62135-002-47)

32 fl oz (946 mL) bottle (NDC 62135-002-94)

4 Quarts (3785 mL) bottle (NDC 62135-002-78)

15 mL Unit Dose Cups (NDC 62135-002-51)

20 Unit Dose Cups of 15 mL each (NDC 62135-002-24)

30 mL Unit Dose Cups (NDC 62135-004-43)

20 Unit Dose Cups of 30 mL each (NDC 62135-004-24)

Lactulose Solution, USP contains 667 mg/mL (10 g/15 mL).

Store at 20° to 25°C (68° to 77°F). [See USP Controlled Room Temperature.] Do not freeze. Keep tightly closed.

Under recommended storage conditions, a normal darkening of color may occur. Such darkening is characteristic of sugar solutions and does not affect therapeutic action. Prolonged exposure to temperatures above 30°C (86°F) or to direct light may cause extreme darkening and turbidity which may be pharmaceutically objectionable. If this condition develops, do not use.

Prolonged exposure to freezing temperatures may cause change to a semi-solid, too viscous to pour. Viscosity will return to normal upon warming to room temperature.

Dispense in original container or in a tight, light-resistant container as defined in the USP, with a child-resistant closure.

Manufactured for:
Chartwell RX, LLC.
Congers, NY 10920

L72121

Rev: 01/2026

PACKAGE LABEL

Lactulose Oral Solution, USP 10 g/15 mL - NDC 62135-002-37 - 237 mL Bottle Label

Lactulose Oral Solution, USP 10 g/15 mL - NDC 62135-002-47 - 473 mL Bottle Label

Lactulose Oral Solution, USP 10 g/15 mL - NDC 62135-002-94 - 946 mL Bottle Label

Lactulose Oral Solution, USP 10 g/15 mL - NDC 62135-002-78 - 3785 mL Bottle Label

Lactulose Oral Solution, USP 10 g/15 mL - NDC 62135-002-51 - 15 mL Unit Dose Cup

Lactulose Oral Solution, USP 20 g/30 mL - NDC 62135-004-43 - 30 mL Unit Dose Cup